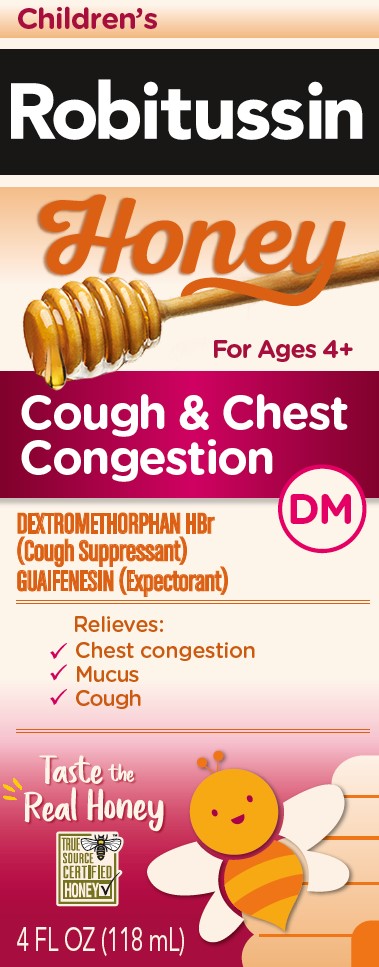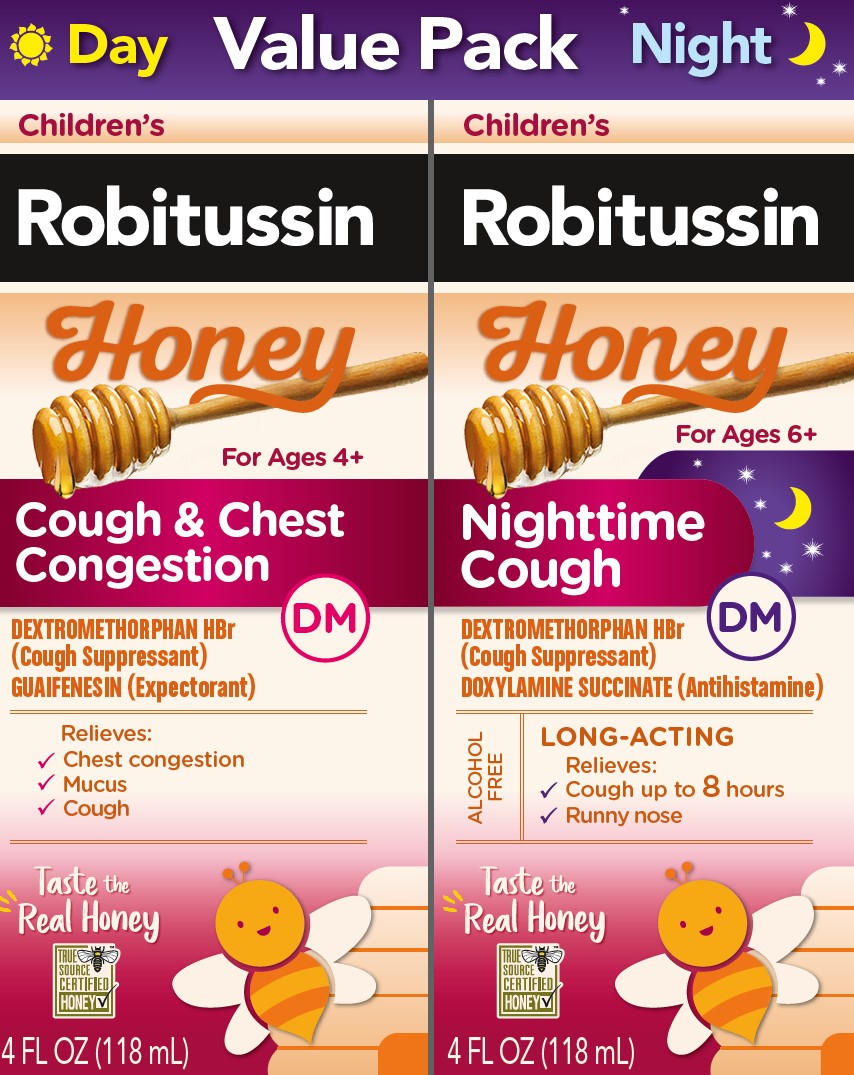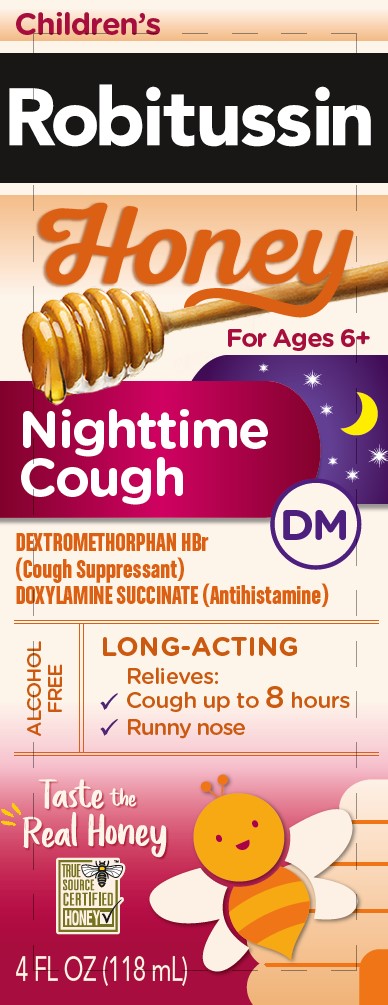 DRUG LABEL: Robitussin

NDC: 0031-2102 | Form: KIT | Route: ORAL
Manufacturer: Haleon US Holdings LLC
Category: otc | Type: HUMAN OTC DRUG LABEL
Date: 20251015

ACTIVE INGREDIENTS: DEXTROMETHORPHAN HYDROBROMIDE 10 mg/10 mL; GUAIFENESIN 100 mg/10 mL; DEXTROMETHORPHAN HYDROBROMIDE 15 mg/10 mL; DOXYLAMINE SUCCINATE 6.25 mg/10 mL
INACTIVE INGREDIENTS: ANHYDROUS CITRIC ACID; CARBOXYMETHYLCELLULOSE SODIUM, UNSPECIFIED; GLYCERIN; LACTIC ACID, UNSPECIFIED FORM; HONEY; POLYETHYLENE GLYCOL, UNSPECIFIED; PROPYLENE GLYCOL; WATER; SODIUM BENZOATE; SODIUM CITRATE, UNSPECIFIED FORM; SODIUM GLUCONATE; SUCRALOSE; XANTHAN GUM; ZINC GLUCONATE; ANHYDROUS CITRIC ACID; CARBOXYMETHYLCELLULOSE SODIUM, UNSPECIFIED; GLYCERIN; LACTIC ACID, UNSPECIFIED FORM; HONEY; POLYETHYLENE GLYCOL, UNSPECIFIED; PROPYLENE GLYCOL; WATER; SODIUM BENZOATE; SODIUM CITRATE, UNSPECIFIED FORM; SODIUM GLUCONATE; SUCRALOSE; XANTHAN GUM; ZINC GLUCONATE

Drug Facts

Active ingredients (in each 10 mL)– Children’s Robitussin Honey Cough & Chest Congestion DM

Dextromethorphan HBr, USP 10 mg

Guaifenesin, USP 100 mg

Purposes –Children’s Robitussin Honey Cough & Chest Congestion DM

Cough Suppressant

Expectorant

Uses– Children’s Robitussin Honey Cough & Chest Congestion DM

- temporarily relieves cough due to minor throat and bronchial irritation as may occur with a cold
- helps loosen phlegm (mucus) and thin bronchial secretions to drain bronchial tube

Warnings– Children’s Robitussin Honey Cough & Chest Congestion DM

Do not use

if you are now taking a prescription monoamine oxidase inhibitor (MAOI) (certain drugs for depression, psychiatric, or emotional conditions, or Parkinson’s disease), or for 2 weeks after stopping the MAOI drug. If you do not know if your prescription drug contains an MAOI, ask a doctor or pharmacist before taking this product.

Ask a doctor before use if you have

- cough that occurs with too much phlegm (mucus)
- cough that lasts or is chronic such as occurs with smoking, asthma, chronic bronchitis, or emphysema

Stop use and ask a doctor if

cough lasts more than 7 days, comes back, or is accompanied by fever, rash, or persistent headache.

These could be signs of a serious condition.

If pregnant or breast-feeding,

ask a health professional before use.

Keep out of reach of children.

In case of overdose, get medical help or contact a Poison Control Center right away.

Directions– Children’s Robitussin Honey Cough & Chest Congestion DM

- do not take more than 6 doses in any 24-hour period
- measure only with dosing cup provided
- keep dosing cup with product
- mL = milliliter

age | dose
children under 4 years | do not use
children 4 to under 6 years | 5 mL every 4 hours
children 6 to under 12 years | 10 mL every 4 hours
adults and children 12 years and over | 20 mL every 4 hours

Other information –Children’s Robitussin Honey Cough & Chest Congestion DM

- each 10 mL contains:sodium 11 mg
- store at 20-25°C (68-77°F). Do not refrigerate.

Inactive ingredients– Children’s Robitussin Honey Cough & Chest Congestion DM

anhydrous citric acid, blueberry juice concentrate, carboxymethylcellulose sodium, glycerin, lactic acid, natural and artificial flavors, natural grade A honey, polyethylene glycol, propylene glycol, purified water, sodium benzoate, sodium citrate, sodium gluconate, sucralose, xanthan gum, zinc gluconate

Questions or comments?– Children’s Robitussin Honey Cough & Chest Congestion DM

call weekdays from 9 AM to 5 PM EST at 1-800-245-1040

Active ingredients (in each 10 mL)– Children’s Robitussin Honey Nighttime Cough DM

Dextromethorphan HBr, USP 15 mg

Doxylamine succinate, USP 6.25 mg

Purposes– Children’s Robitussin Honey Nighttime Cough DM

Cough suppressant

Antihistamine

Uses –Children’s Robitussin Honey Nighttime Cough DM

- temporarily relieves cough due to minor throat and bronchial irritation as may occur with a cold
- temporarily relieves these symptoms due to hay fever or other upper respiratory allergies:
  - runny nose
  - sneezing
  - itchy, watery eyes
  - itching of the nose or throat
- controls the impulse to cough to help you sleep

Warnings –Children’s Robitussin Honey Nighttime Cough DM

Do not use

- to sedate a child or to make a child sleepy
- if you are now taking a prescription monoamine oxidase inhibitor (MAOI) (certain drugs for depression, psychiatric, or emotional conditions, or Parkinson’s disease), or for 2 weeks after stopping the MAOI drug. If you do not know if your prescription drug contains an MAOI, ask a doctor or pharmacist before taking this product.

Ask a doctor before use if you have

- trouble urinating due to an enlarged prostate gland
- glaucoma
- a cough that occurs with too much phlegm (mucus)
- a breathing problem or chronic cough that lasts or as occurs with smoking, asthma, chronic bronchitis or emphysema

Ask a doctor or pharmacist before use if you are

taking sedatives or tranquilizers

When using this product

- do not use more than directed
- marked drowsiness may occur
- avoid alcoholic drinks
- alcohol, sedatives, and tranquilizers may increase drowsiness
- be careful when driving a motor vehicle or operating machinery
- excitability may occur, especially in children

Stop use and ask a doctor if

cough lasts more than 7 days, comes back, or is accompanied by fever, rash, or persistent headache.

These could be signs of a serious condition.

If pregnant or breast-feeding,

ask a health professional before use.

Keep out of reach of children.

In case of overdose, get medical help or contact a Poison Control Center right away.

Directions –Children’s Robitussin Honey Nighttime Cough DM

- measure only with dosing cup provided
- keep dosing cup with product
- mL = milliliter
- do not take more than 4 doses in any 24-hour period

age | dose
children under 6 years | do not use
children 6 to 12 years | 10 mL every 6 hours
adults and children 12 years and older | 20 mL every 6 hours

Other information–Children’s Robitussin Honey Nighttime Cough DM

- each 10 mL contains:sodium 10 mg
- store at 20-25°C (68-77°F)

Inactive ingredients–Children’s Robitussin Honey Nighttime Cough DM

anhydrous citric acid, blueberry juice concentrate, carboxymethylcellulose sodium, glycerin, lactic acid, natural and artificial flavors, natural grade A honey, polyethylene glycol, propylene glycol, purified water, sodium benzoate, sodium citrate, sodium gluconate, sucralose, xanthan gum, zinc gluconate

Questions or comments? –Children’s Robitussin Honey Nighttime Cough DM

call weekdays from 9 AM to 5 PM EST at 1-800-245-1040

Additional Information

Packaged with Tamper-Evident bottle cap. Do Not Use if breakable ring is separated or missing.

Do not take both products within 6 hours of each other.

Children’s

Robitussin

Honey

This dynamic duo combines the great taste of natural honey with the effective cough relief of Robitussin you trust to help your child feel better.

Made with Real Honey

TRUE SOURCE CERTIFIED HONEY

Gluten Free

No Artificial Colors

PARENTS:

Learn about teen medicine abuse

www.StopMedicineAbuse.org

Principal Display Panel – Children’s Robitussin Honey Day Night Value Pack

Value Pack

Day Night

Children’s

Robitussin

Honey

For Ages 4+

Cough & Chest Congestion DM

DEXTROMETHORPHAN HBr

(Cough Suppressant)

GUAIFENESIN (Expectorant)

Relieves:

- Chest congestion
- Mucus
- Cough

Taste the Real Honey

TRUE SOURCE CERTIFIED HONEY

4 FL OZ (118 mL)

Children’s

Robitussin

Honey

For ages 6+

Nighttime Cough DM

DEXTROMETHORPHAN HBr

(Cough Suppressant)

DOXYLAMINE SUCCINATE (Antihistamine)

ALCOHOL FREE

LONG-ACTING

Relieves:

- Cough up to 8hours
- Runny nose

Taste the Real Honey

TRUE SOURCE CERTIFIED HONEY

4 FL OZ (118 mL)

Principal Display Panel –Children’s Robitussin Honey Cough & Chest Congestion DM

Children’s

Robitussin

Honey

For Ages 4+

Cough & Chest Congestion DM

DEXTROMETHORPHAN HBr

(Cough Suppressant)

GUAIFENESIN (Expectorant)

Relieves:

- Chest congestion
- Mucus
- Cough

Taste the Real Honey

TRUE SOURCE CERTIFIED HONEY

4 FL OZ (118 mL)

Principal Display Panel – Children’s Robitussin Honey Nighttime Cough DM

Children’s

Robitussin

Honey

For ages 6+

Nighttime Cough DM

DEXTROMETHORPHAN HBr

(Cough Suppressant)

DOXYLAMINE SUCCINATE (Antihistamine)

ALCOHOL FREE

LONG-ACTING

Relieves:

- Cough up to 8hours
- Runny nose

Taste the Real Honey

TRUE SOURCE CERTIFIED HONEY

4 FL OZ (118 mL)